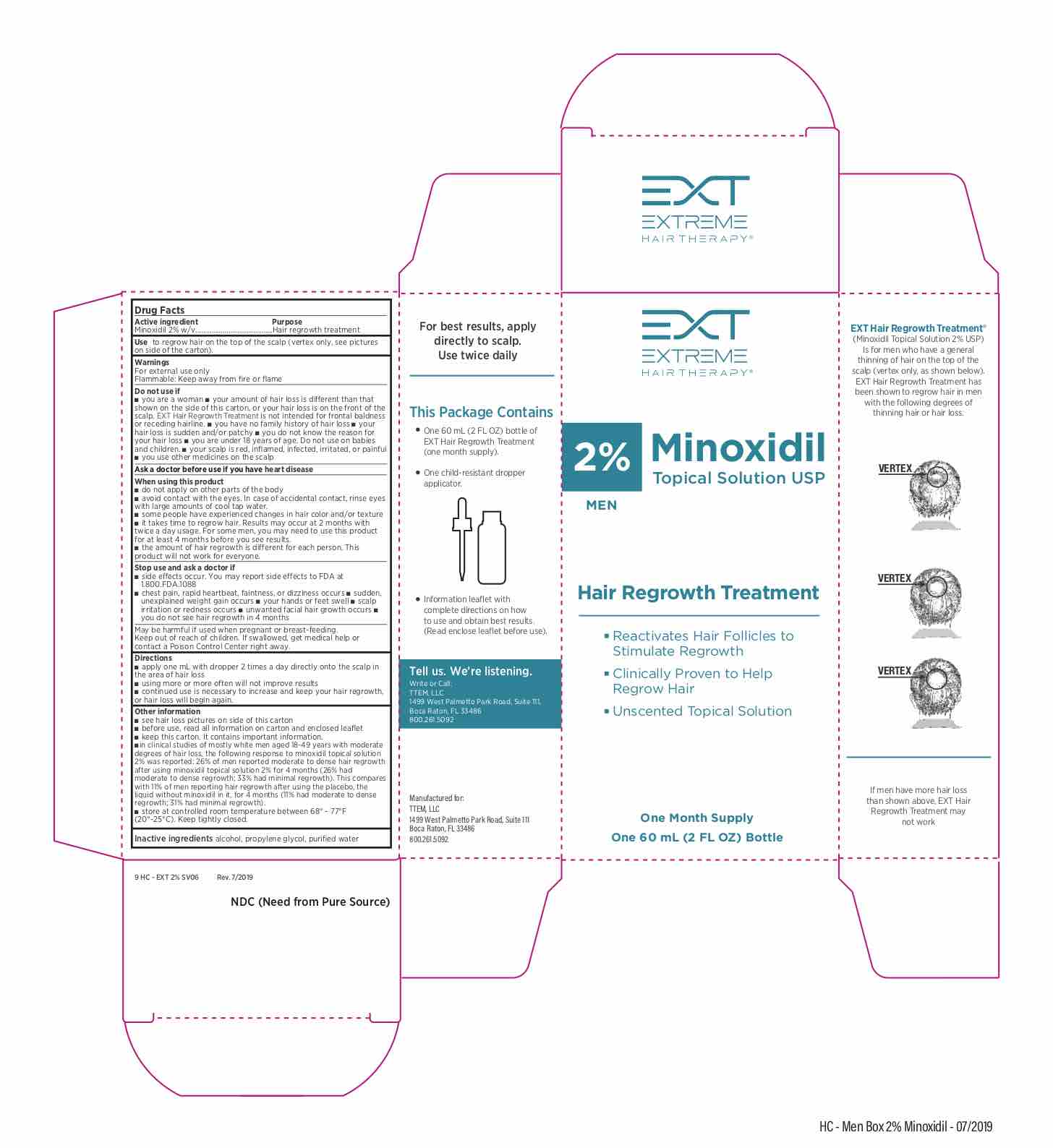 DRUG LABEL: EXT Hair Regrowth Treatment for Men 2%
NDC: 70150-002 | Form: SOLUTION
Manufacturer: TTEM, LLC
Category: otc | Type: HUMAN OTC DRUG LABEL
Date: 20230118

ACTIVE INGREDIENTS: MINOXIDIL 2 g/100 mL
INACTIVE INGREDIENTS: ISOPROPYL ALCOHOL; PROPYLENE GLYCOL; WATER

EXT Hair Regrowth Treatment for Men 2%

ACTIVE INGREDIENT

Minoxidil 2% w/v

USE

Use to regrow hair on the top of the scalp (vertex only, see pictures on side of the carton).

PURPOSE

Hair regrowth treatment

WARNINGS

For external use only

Flammable: Keep away from fire or flame

Do not use if

■ you are a woman ■ your amount of hair loss is dierent than that

shown on the side of this carton, or your hair loss is on the front of the

scalp. EXT Hair Regrowth Treatment is not intended for frontal baldness

or receding hairline. ■ you have no family history of hair loss ■ your

hair loss is sudden and/or patchy ■ you do not know the reason for

your hair loss ■ you are under 18 years of age. Do not use on babies

and children. ■ your scalp is red, inflamed, infected, irritated, or painful

■ you use other medicines on the scalp

Ask a doctor before use if you have heart disease

When using this product

■ do not apply on other parts of the body

■ avoid contact with the eyes. In case of accidental contact, rinse eyes

with large amounts of cool tap water.

■ some people have experienced changes in hair color and/or texture

■ it takes time to regrow hair. Results may occur at 2 months with

twice a day usage. For some men, you may need to use this product

for at least 4 months before you see results.

■ the amount of hair regrowth is dierent for each person. This

product will not work for everyone.

Stop use and ask a doctor if

■ side eects occur. You may report side eects to FDA at

1.800.FDA.1088

■ chest pain, rapid heartbeat, faintness, or dizziness occurs ■ sudden,

unexplained weight gain occurs ■ your hands or feet swell ■ scalp

irritation or redness occurs ■ unwanted facial hair growth occurs ■

you do not see hair regrowth in 4 months

PREGNANCY OR BREAST FEEDING

May be harmful if used when pregnant or breast-feeding.

Keep out of reach of children. If swallowed, get medical help or contact a Poison Control Center right away.

DIRECTIONS

■ apply one mL with dropper 2 times a day directly onto the scalp in

the area of hair loss

■ using more or more often will not improve results

■ continued use is necessary to increase and keep your hair regrowth,

or hair loss will begin again.

Other information

■ see hair loss pictures on side of this carton

■ before use, read all information on carton and enclosed leaflet

■ keep this carton. It contains important information.

■in clinical studies of mostly white men aged 18-49 years with moderate

degrees of hair loss, the following response to minoxidil topical solution

2% was reported: 26% of men reported moderate to dense hair regrowth

after using minoxidil topical solution 2% for 4 months (26% had

moderate to dense regrowth; 33% had minimal regrowth). This compares

with 11% of men reporting hair regrowth after using the placebo, the

liquid without minoxidil in it, for 4 months (11% had moderate to dense

regrowth; 31% had minimal regrowth).

■ store at controlled room temperature between 68° - 77°F

(20°-25°C). Keep tightly closed.

Inactive ingredients

alcohol, propylene glycol, purified water